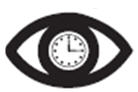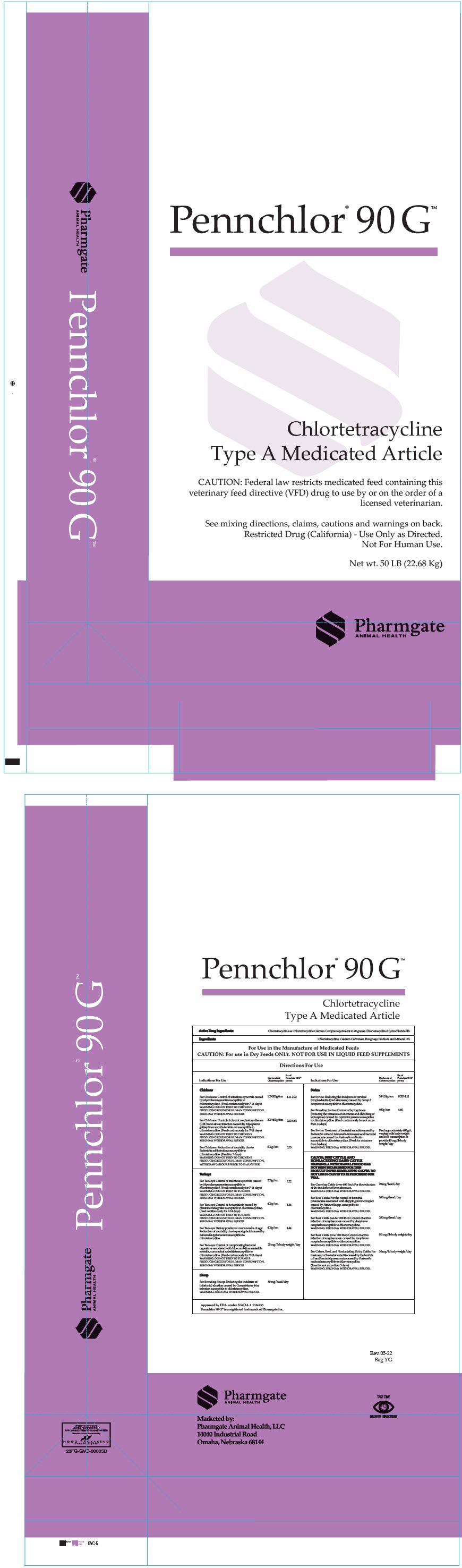 DRUG LABEL: Pennchlor 90G
NDC: 51429-091 | Form: GRANULE
Manufacturer: Pharmgate Animal Health
Category: animal | Type: VFD TYPE A MEDICATED ARTICLE ANIMAL DRUG LABEL
Date: 20230210

ACTIVE INGREDIENTS: Chlortetracycline Calcium 198 g/1 kg
INACTIVE INGREDIENTS: Calcium Carbonate; Mineral Oil

Pennchlor® 90 G™

Chlortetracyline
Type A Medicated Article

DESCRIPTION

Active Drug Ingredients: Chlortetracycline as Chlortetracycline Calcium Complex equivalent to 90 grams Chlortetracycline Hydrochloride/lb.

Ingredients: Chlortetracycline, Calcium Carbonate, Roughage Products and Mineral Oil.

For Use in the Manufacture of Medicated Feeds.

CAUTION: For use in Dry Feeds ONLY. NOT FOR USE IN LIQUID FEED SUPPLEMENTS

Directions For Use

Indications For Use | Use Level of Chlortetracycline | lbs. of Pennchlor 90 G® per ton
Chickens
For Chickens: Control of infectious synovitis caused by Mycoplasma synoviae susceptible to chlortetracycline. (Feed continuously for 7 - 14 days) | 100-200 g/ton | 1.11 – 2.22
WARNING: DO NOT FEED TO CHICKENS PRODUCING EGGS FOR HUMAN CONSUMPTION. ZERO-DAY WITHDRAWAL PERIOD.
For Chickens: Control of chronic respiratory disease (CRD) and air sac infection caused by Mycoplasma gallisepticum and Escherichia coli susceptible to chlortetracycline. (Feed continuously for 7 - 14 days). | 200-400 g/ton | 2.22 – 4.44
WARNING: DO NOT FEED TO CHICKENS PRODUCING EGGS FOR HUMAN CONSUMPTION. ZERO-DAY WITHDRAWAL PERIOD.
For Chickens: Reduction of mortality due to Escherichia coli infections susceptible to chlortetracycline (Feed for 5 days). | 500 g/ton | 5.55
WARNING: DO NOT FEED TO CHICKENS PRODUCING EGGS FOR HUMAN CONSUMPTION. WITHDRAW 24 HOURS PRIOR TO SLAUGHTER.
Turkeys
For Turkeys: Control of infectious synovitis caused by Mycoplasma synoviae susceptible to chlortetracycline (Feed continuously for 7 - 14 days) | 200 g/ton | 2.22
WARNING: DO NOT FEED TO TURKEYS PRODUCING EGGS FOR HUMAN CONSUMPTION. ZERO-DAY WITHDRAWAL PERIOD.
For Turkeys: Control of hexamitiasis caused by Hexamita meleagrides susceptible to chlortetracycline. (Feed continuously for 7 - 14 days). | 400 g/ton | 4.44
WARNING: DO NOT FEED TO TURKEYS PRODUCING EGGS FOR HUMAN CONSUMPTION. ZERO-DAY WITHDRAWAL PERIOD.
For Turkeys: Turkey poults not over 4 weeks of age: Reduction of mortality due to paratyphoid caused by Salmonella typhimurium susceptible to chlortetracycline. | 400 g/ton | 4.44
For Turkeys: Control of complicating bacterial organisms associated with bluecomb (transmissible enteritis, coronaviral enteritis) susceptible to chlortetracycline. (Feed continuously for 7 - 14 days) | 25 mg/lb body weight/day
WARNINGS: DO NOT FEED TO TURKEYS PRODUCING EGGS FOR HUMAN CONSUMPTION. ZERO-DAY WITHDRAWAL PERIOD.
Swine
For Swine: Reducing the incidence of cervical lymphadenitis (jowl abscesses) caused by Group E Streptococci susceptible to chlortetracycline. | 50-100 g/ton | 0.555 – 1.11
For Breeding Swine: Control of leptospirosis (reducing the instances of abortions and shedding of leptospirae) caused by Leptospira pomona susceptible to chlortetracycline. (Feed continuously for not more than 14 days) | 400 g/ton | 4.44
For Swine: Treatment of bacterial enteritis caused by Escherichia coli and Salmonella choleraesuis and bacterial pneumonia caused by Pasteurella multocida susceptible to chlortetracycline. (Feed for not more than 14 days.) | Feed approximately 400 g/t, varying with body weight and feed consumption to provide 10 mg/lb body weight/day.
WARNING: ZERO-DAY WITHDRAWAL PERIOD.
CALVES, BEEF CATTLE, AND NONLACTATING DAIRY CATTLE WARNING: A WITHDRAWAL PERIOD HAS NOT BEEN ESTABLISHED FOR THIS PRODUCT IN PRE-RUMINATNG CALVES. DO NOT USE IN CALVES TO BE PROCESSED FOR VEAL.
For Growing Cattle (over 400 lbs.): For the reduction of the incidence of liver abscesses. | 70 mg/head/day
WARNING: ZERO-DAY WITHDRAWAL PERIOD.
For Beef Cattle: For the control of bacterial pneumonia associated with shipping fever complex caused by Pasteurella spp. susceptible to chlortetracycline | 350 mg/head/day
WARNING: ZERO-DAY WITHDRAWAL PERIOD.
For Beef Cattle (under 700 lbs.): Control of active infection of anaplasmosis caused by Anaplasma marginale susceptible to chlortetracycline. | 350 mg/head/day
WARNING: ZERO-DAY WITHDRAWAL PERIOD.
For Beef Cattle (over 700 lbs.): Control of active infection of anaplasmosis caused by Anaplasma marginale susceptible to chlortetracycline. | 0.5 mg/ lb. body weight/day
WARNING: ZERO-DAY WITHDRAWAL PERIOD.
For Calves, Beef, and Nonlactating Dairy Cattle: For treatment of bacterial enteritis caused by Escherichia coli and bacterial pneumonia caused by Pasteurella multocida susceptible to chlortetracycline. (Treat for not more than 5 days) | 10 mg/lb. body weight/day
WARNING: ZERO-DAY WITHDRAWAL PERIOD.
Sheep
For Breeding Sheep: Reducing the incidence of (vibrionic) abortion caused by Campylobacter fetus infections susceptible to chlortetracycline. | 80 mg/head/day
WARNING: ZERO-DAY WITHDRAWAL PERIOD.
Approved by FDA under NADA # 138-935
Pennchlor 90 G® is a registered trademark of Pharmgate Inc.

Marketed by:
Pharmgate Animal Health, LLC
14040 Industrial Road
Omaha, NE 68144

Take Time Observe Directions

PRINCIPAL DISPLAY PANEL - 22.68 Kg Bag Label

Pennchlor® 90 G™

Chlortetracycline

Type A Medicated Article

CAUTION: Federal law restricts medicated feed containing this
veterinary feed directive (VFD) drug to use by or on the order of a
licensed veterinarian.

See mixing directions, claims, cautions and warnings on back.
Restricted Drug (California) - Use Only as Directed.
Not For Human Use.

Net wt. 50 LB (22.68 Kg)

Pharmgate
ANIMAL HEALTH